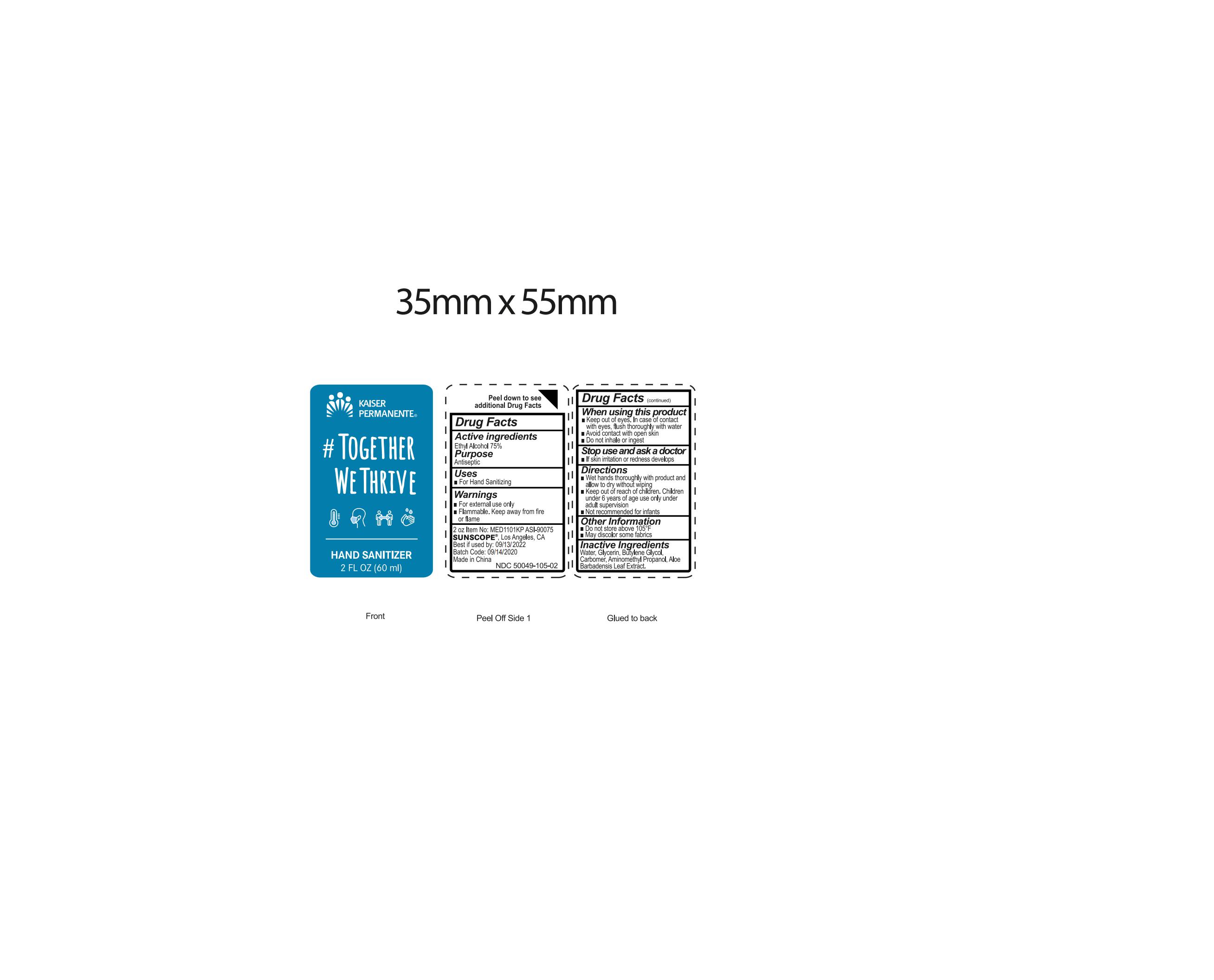 DRUG LABEL: hand sanitizer
NDC: 50049-105 | Form: GEL
Manufacturer: QUANZHOU BESTHOPE HOUSEHOLD PRODUCTS CO.,LTD.
Category: otc | Type: HUMAN OTC DRUG LABEL
Date: 20200930

ACTIVE INGREDIENTS: ALCOHOL 75 mL/100 mL
INACTIVE INGREDIENTS: WATER; GLYCERIN; ALOE VERA LEAF; AMINOMETHYL PROPANEDIOL; BUTYLENE GLYCOL; CARBOMER HOMOPOLYMER, UNSPECIFIED TYPE

50049-105 Hand Sanitizer 75% Ethyl Alcohol

Active Ingredient

Ethyl Alcohol 75%

Purpose

Antiseptic

Use

For hand Sanitizing

WARNINGS

■For external use only
Flammable. Keep away from fire or flame
When using this product
n Keep out of eyes. In case of contact with eyes
flush thoroughly with water
■Avoid contact with open skin
1 Do not inhale or ingest
Stop use and ask a doctor
If skin iritation or redness develops

Keep out of reach of children
If swallowed , get medical help or contact a Poison Control Center right away

Directions

Wet hands thoroughly with product and allow to dry without wiping

Children under 6 years of age use only under adult supervision.

Not recommended for infants

Inactive ingredients

Water,Glycerin,Butylene Glycol,
Carbomer,Aminomethyl Propanol,Aloe
Barbadensis Leaf Extract.